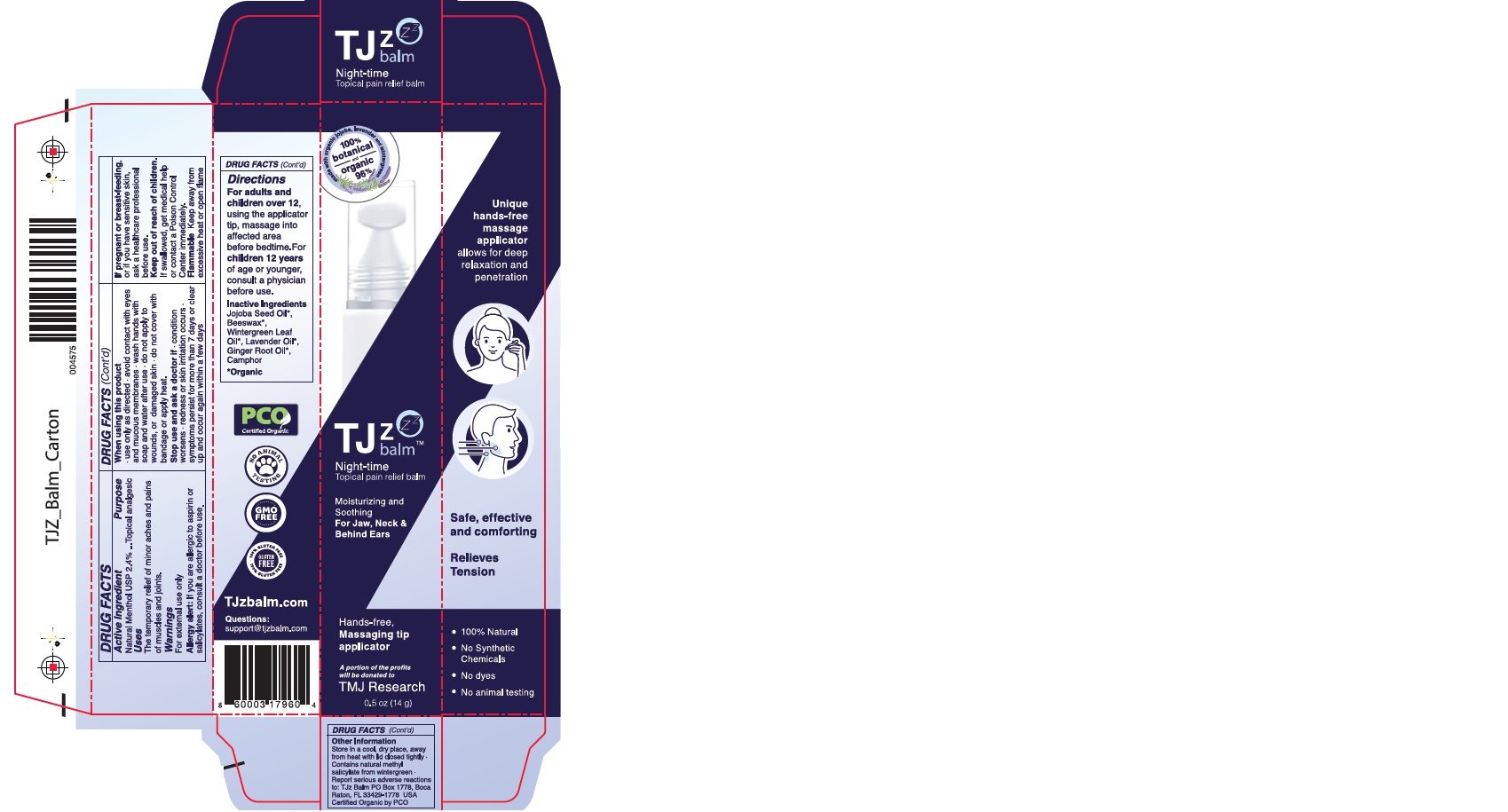 DRUG LABEL: TJz Night-time Topical Pain Relief Balm
NDC: 73668-001 | Form: OINTMENT
Manufacturer: LAB-O Corp
Category: otc | Type: HUMAN OTC DRUG LABEL
Date: 20200927

ACTIVE INGREDIENTS: MENTHOL 24 mg/1 g
INACTIVE INGREDIENTS: JOJOBA OIL; LAVENDER OIL; GINGER OIL; YELLOW WAX; METHYL SALICYLATE; CAMPHOR (NATURAL)

TJz Night-time Topical Pain Relief Balm

Active Ingredient

Natural Menthol USP 2.4%

Purpose

Topical analgesic

Uses

The temporary relief of minor aches and pains of muscles and joints.

Warnings

For external use only

Allergy alert: If you are allergic to aspirin or salicylates, consult a doctor before use

When using this product

- use only as directed
- avoid contact with eyes and mucous membranes
- wash hands with soap and water after use
- do not apply to wounds, or damaged skin
- do not cover with bandage or apply heat

Stop use and ask a doctor if

- condition worsens
- redness or skin irritation occurs
- symptoms persist for more than 7 days or clear up and occur again within a few days

If pregnant or breast-feeding

or if you have sensitive skin, ask a healthcare professional before use

Keep out of reach of children.

If swallowed, get medical help or contact a Poison Control Center immediately.

Flammable

Keep away from excessive heat or open flame

Directions

For adults and children over 12, using the applicator tip, massage into affected area before bedtime. For children 12 years of age or younger, consult a physician before use.

Inactive Ingredients

Jojoba Seed Oil*, Beeswax*, Wintergreen Leaf Oil*, Lavender Oil*, Ginger Root Oil*, Camphor

*Organic

Other Information

Store in a cool, dry place, away from heat with lid closed tightly. Contains natural methyl salicylate from wintergreen. Report serious adverse reactions to: TJz Balm PO Box 1778, Boca Raton, FL 33429-1778 USA

Certified Organic by PCO

Company Information

TJzbalm.com

Questions: support@tjzbalm.com

Product Packaging

TJz balm

Night-time

Topical pain relief balm

Moisturizing and

Soothing

For Jaw, Neck &

Behind Ears

Hands-free,

Massaging tip applicator

A portion of the profits

will be donated to

TMJ Research

0.5 oz (14 g)